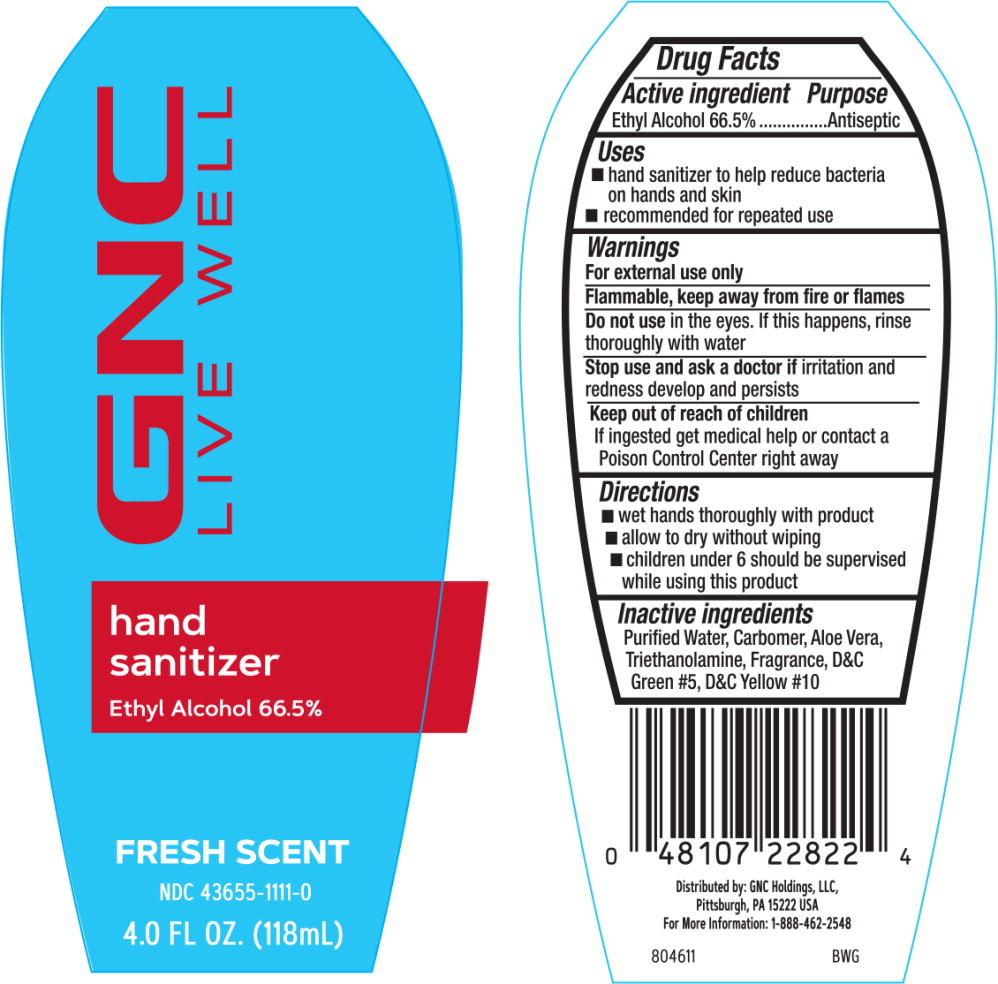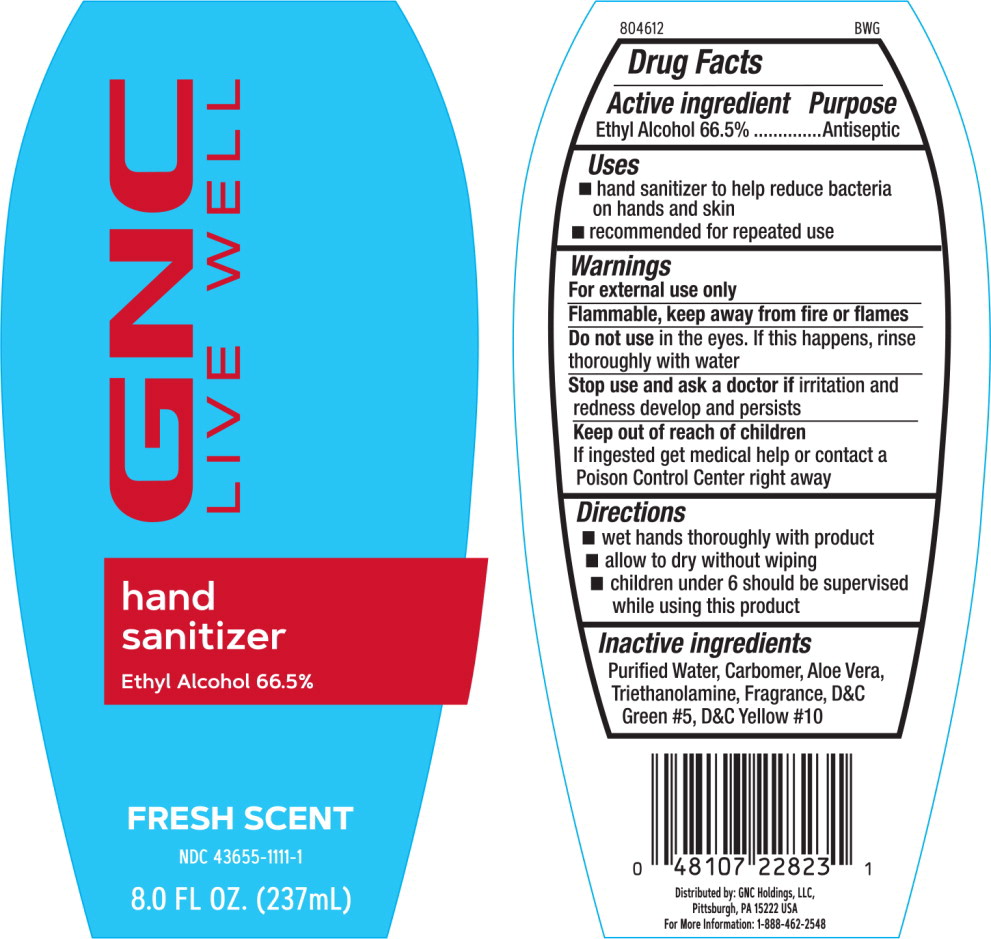 DRUG LABEL: GNC Instant Hand Sanitizer
NDC: 43655-1111 | Form: GEL
Manufacturer: GNC Holdings LLC
Category: otc | Type: HUMAN OTC DRUG LABEL
Date: 20230131

ACTIVE INGREDIENTS: ALCOHOL 66.5 mL/100 mL
INACTIVE INGREDIENTS: ALOE VERA LEAF; CARBOMER HOMOPOLYMER, UNSPECIFIED TYPE; D&C GREEN NO. 5; D&C YELLOW NO. 10; WATER; TROLAMINE

Drug Facts

Active ingredient

Ethyl Alcohol 66.5%

Purpose

Antiseptic

Uses

- hand sanitizer to help reduce bacteria on hands and skin
- recommended for repeated use

Warnings

For external use only

Flammable, keep away from fire or flames

Do not use in the eyes. If this happens, rinse thoroughly with water

Stop use and ask a doctor if irritation and redness develop and persists

Keep out of reach of children

If ingested get medical help or contact a Poison Control Center right away

Directions

- wet hands thoroughly with product
- allow to dry without wiping
- children under 6 should be supervised while using this product

Inactive ingredients

Purified Water, Carbomer, Aloe Vera, Triethanolamine, Fragrance, D&C Green #5, D&C Yellow #10

Principal Display Panel - 118 mL Bottle Label

GNC
LIVE WELL

hand
sanitizer

Ethyl Alcohol 66.5%

FRESH SCENT

NDC 43655-1111-0

4.0 FL. OZ. (118 mL)

Principal Display Panel - 237 mL Bottle Label

GNC
LIVE WELL

hand
sanitizer

Ethyl Alcohol 66.5%

FRESH SCENT

NDC 43655-1111-1

8.0 FL. OZ. (237 mL)